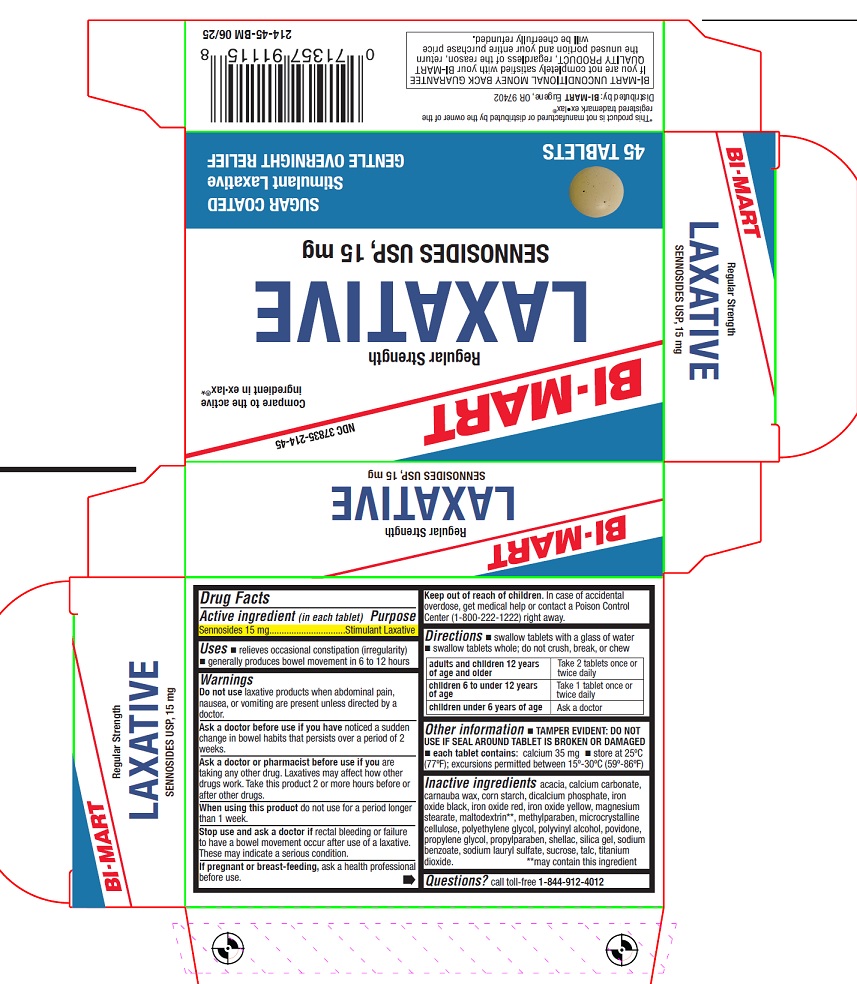 DRUG LABEL: Laxative

NDC: 37835-214 | Form: TABLET, SUGAR COATED
Manufacturer: Bi-Mart
Category: otc | Type: HUMAN OTC DRUG LABEL
Date: 20250801

ACTIVE INGREDIENTS: SENNOSIDES 15 mg/1 1
INACTIVE INGREDIENTS: ACACIA; CALCIUM CARBONATE; CARNAUBA WAX; STARCH, CORN; DIBASIC CALCIUM PHOSPHATE DIHYDRATE; FERROSOFERRIC OXIDE; FERRIC OXIDE RED; FERRIC OXIDE YELLOW; MAGNESIUM STEARATE; METHYLPARABEN; MICROCRYSTALLINE CELLULOSE; POLYETHYLENE GLYCOL, UNSPECIFIED; POLYVINYL ALCOHOL, UNSPECIFIED; POVIDONE, UNSPECIFIED; PROPYLENE GLYCOL; PROPYLPARABEN; SHELLAC; SILICON DIOXIDE; SODIUM BENZOATE; SODIUM LAURYL SULFATE; SUCROSE; TALC; TITANIUM DIOXIDE

Active ingredient (in each tablet)

Sennosides 15 mg

Purpose

Stimulant Laxative

Uses

- relieves occasional constipation (irregularity)
- generally produces bowel movement in 6 to 12 hours

Warnings

Do not use

laxative products when abdominal pain, nausea, or vomiting are present unless directed by a doctor.

Ask a doctor before use if you have

noticed a sudden change in bowel habits that persists over a period of 2 weeks.

Ask a doctor or pharmacist before use if you

are taking any other drug. Laxatives may affect how other drugs work. Take this product 2 or more hours before or after other drugs.

When using this product

do not use for a period longer than 1 week.

Stop use and ask a doctor if

rectal bleeding or failure to have a bowel movement occur after use of a laxative. These may bindicate a serious condition.

If pregnant or breast-feeding,

ask a health professional before use.

Keep out of reach of children.

In case of accidental overdose, get medical help or contact a Poison Control Center (1-800-222-1222) right away.

Directions

- swallow tablets with a glass of water
- swallow tablets whole; do not crush, break, or chew

adults and children 12 years of age and older | Take 2 tablets once or twice daily
children 6 to under 12 years of age | Take 1 tablet once or twice daily
children under 6 years of age | Ask a doctor

Other information

- TAMPER EVIDENT: DO NOT USE IF SEAL AROUND TABLET IS BROKEN OR DAMAGED
- each tablet contains:calcium 35 mg
- store at 25°C (77°F); excursions permitted between 15°-30°C (59°-86°F)

Inactive ingredients

acacia, calcium carbonate, carnauba wax, corn starch, dicalcium phosphate, iron oxide black, iron oxide red, iron oxide yellow, magnesium stearate, maltodextrin**, methylparaben, microcrystalline cellulose, polyethylene glycol, polyvinyl alcohol, povidone, propylene glycol, propylparaben, shellac, silica gel, sodium benzoate, sodium lauryl sulfate, sucrose, talc, titanium dioxide. **may contain this ingredient

Questions?

call toll-freee 1-844-912-4012